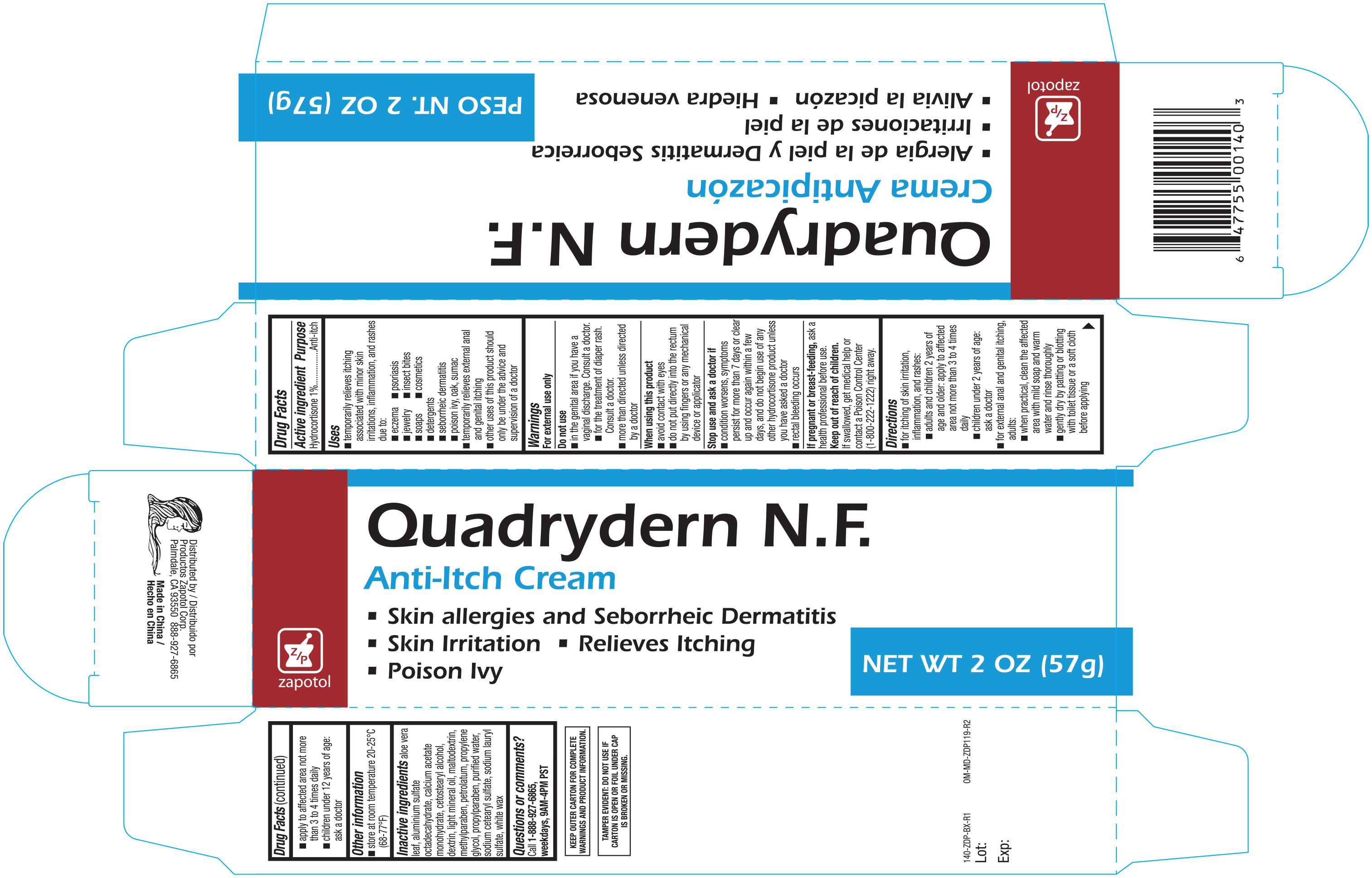 DRUG LABEL: Quadrydern
NDC: 59428-403 | Form: CREAM
Manufacturer: Productos Zapotol Corp
Category: otc | Type: HUMAN OTC DRUG LABEL
Date: 20251021

ACTIVE INGREDIENTS: HYDROCORTISONE 10 mg/1 g
INACTIVE INGREDIENTS: PETROLATUM; WATER; METHYLPARABEN; CALCIUM ACETATE MONOHYDRATE; SODIUM LAURYL SULFATE; MALTODEXTRIN; ALUMINIUM SULFATE OCTADECAHYDRATE; SODIUM CETOSTEARYL SULFATE; WHITE WAX; ALOE VERA LEAF; CETOSTEARYL ALCOHOL; ICODEXTRIN; PROPYLENE GLYCOL; PROPYLPARABEN; LIGHT MINERAL OIL

Quadrydern N.F. Anti-itch Cream 2oz 140A

Active ingredient Purpose

Hydrocortisone 1%..................................................................Anti-itch

Uses

- temporarily relieves itching associated with minor skin irritations, inflammation, and rashes due to: eczema, psoriasis, jewelry, insect bites, soaps, cosmetics, detergents, seborrheic dermatitis, poison ivy, oak, sumac
- temporarily relieves external anal and genital itching
- other uses of this product should be only under the advice and supervision of a doctor

Warnings For external use only

Do not use

- in the genital area if you have a vaginal discharge. Consult a doctor.
- for the treatment of diaper rash. Consult a doctor.
- more than directed unless directed by a doctor.

When using this product

- avoid contact with the eyes
- do not put this product into the rectum by using fingers or any mechanical device or applicator.

Stop use and ask a doctor if

- condition worsens, symptoms persist for more than 7 days or clear up and occur again within a few days and do not begin use of any other hydrocortisone product unless you have consulted a doctor
- rectal bleeding occurs

PREGNANCY OR BREAST FEEDING

If pregnant or breast-feeding, ask a health professional before use.

Keep out of reach of children.

If swallowed, get medical help or contact a Poison Control Center (1-800-222-1222) right away.

Directions

- for itching of skin irritation, inflammation, and rashes:
- adults and children 2 years of age and older: apply to affected area not more than 3 to 4 times daily.
- children under 2 years of age: ask a doctor
- Adults: for external anal itching:
- for external anal and genital itching, adults:
- when practical, clean the affected area with mild soap and warm water and rinse thoroughly
- gently dry by patting or blotting with toilet tissue or a soft cloth before applying
- apply to affected area not more than 3 to 4 times daily
- children under 12 years of age: ask a doctor

Other information

- Store at room temperature 20°-25°C (68°-77°F)

INACTIVE INGREDIENT

Inactive ingredients aloe vera leaf, aluminum sulfate octadecahydrate, calcium acetate monohydrate, cetostearyl alcohol, dextrin, light mineral oil, maltodextrin, methylparaben, petrolatum, propylene glycol, propylparaben, purified water, sodium cetearyl sulfate, sodium lauryl sulfate, white wax

DOSAGE AND ADMINISTRATION

Distributed By:

Productos Zapotol Corp.

Palmdale, CA 93550

Made in China